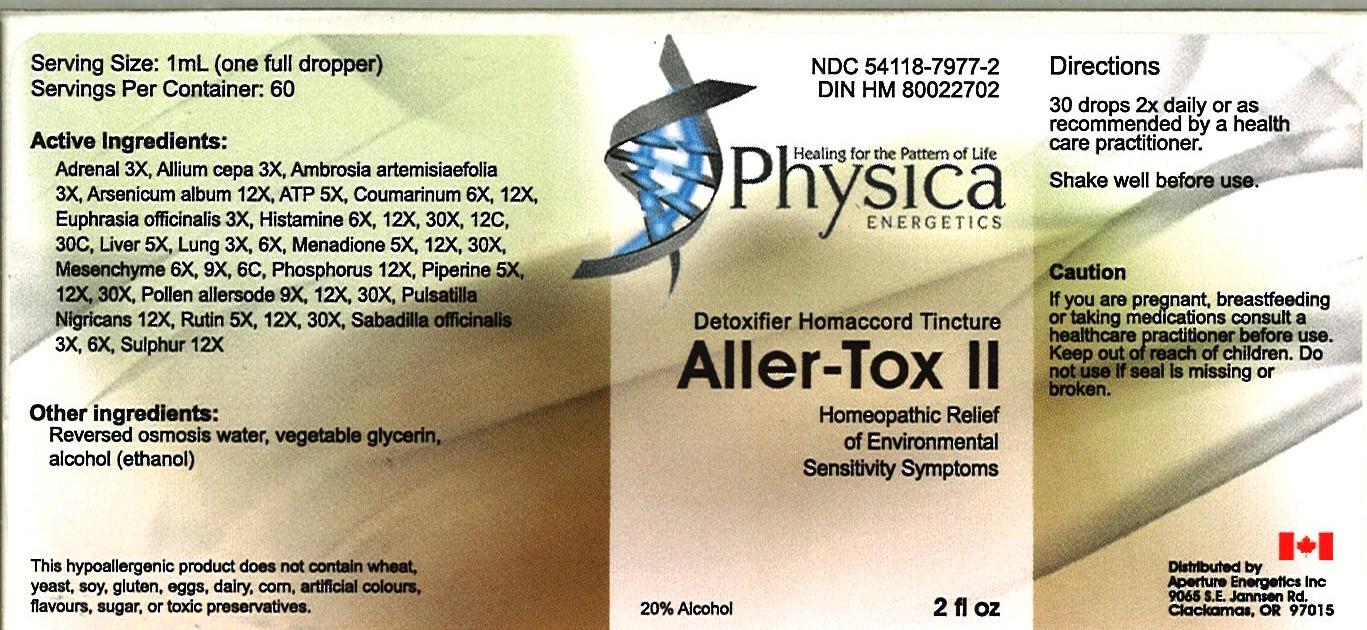 DRUG LABEL: Aller - Tox 11
NDC: 54118-7977 | Form: SOLUTION/ DROPS
Manufacturer: ABCO Laboratories, Inc
Category: homeopathic | Type: HUMAN OTC DRUG LABEL
Date: 20121128

ACTIVE INGREDIENTS: BOS TAURUS ADRENAL GLAND 3 [hp_X]/60 mL; ONION 3 [hp_X]/60 mL; AMBROSIA ARTEMISIIFOLIA 3 [hp_X]/60 mL; ARSENIC TRIOXIDE 12 [hp_X]/60 mL; ADENOSINE TRIPHOSPHATE 5 [hp_X]/60 mL; COUMARIN 6 [hp_X]/60 mL; EUPHRASIA STRICTA 3 [hp_X]/60 mL; HISTAMINE 6 [hp_X]/60 mL; BEEF LIVER 5 [hp_X]/60 mL; BEEF LUNG 3 [hp_X]/60 mL; MENADIONE 5 [hp_X]/60 mL; BOS TAURUS MESENCHYME 6 [hp_X]/60 mL; PHOSPHORUS 12 [hp_X]/60 mL; PIPERINE 5 [hp_X]/60 mL; HYALURONIDASE 9 [hp_X]/60 mL; PULSATILLA PRATENSIS 12 [hp_X]/60 mL; RUTIN 5 [hp_X]/60 mL; SCHOENOCAULON OFFICINALE SEED 3 [hp_X]/60 mL; SULFUR 12 [hp_X]/60 mL
INACTIVE INGREDIENTS: WATER; GLYCERIN; ALCOHOL

Aller - Tox 11 Homeopathic Liquid

Active Ingredients:

Adrenal 3X,

Allium cepa 3X

Ambrosia artemisiaefolia 3X

Arsenicum album 12X

ATP 5X

Coumarinum 6X, 12X

Euphrasia officinalis 3X

Histamine 6X, 12X, 30X, 12C, 30C

Liver 5X

Lung 3X, 6X

Menadione 5X, 12X, 30X

Mesenchyme 6X, 9X, 6C

Phosphorus 12X

Piperine 5X, 12X, 30X

Pollen allersode 9X, 12X, 30X

Pulsatilla Nigicans 12X

Rutin 5X, 12X, 30X

Sabadilla officinalis 3X, 6X

Sulphur 12X

PURPOSE

- Homeopathic Relief of Environmental Sensitivity Symptoms

- Keep out of reach of children

INDICATIONS AND USAGE

- 30 drops 2X daily
- or as recommended by a health care practitioner
- Shake well before use.

WARNINGS

- If you are pregnant, breastfeeding or taking medications consult a healthcare practitioner before use.
- Keep out of reach of children.
- Do not use if seal is missing or broken.

DOSAGE AND ADMINISTRATION

- 30 drops 2X daily
- or as recommended by a health care practitioner
- Shake well before use.

INACTIVE INGREDIENT

- Reversed osmosis water
- vegetable glycerin
- alcohol (ethanol)

PACKAGE LABEL

- bottle image/jpeg
- allertoxlabel.jpg